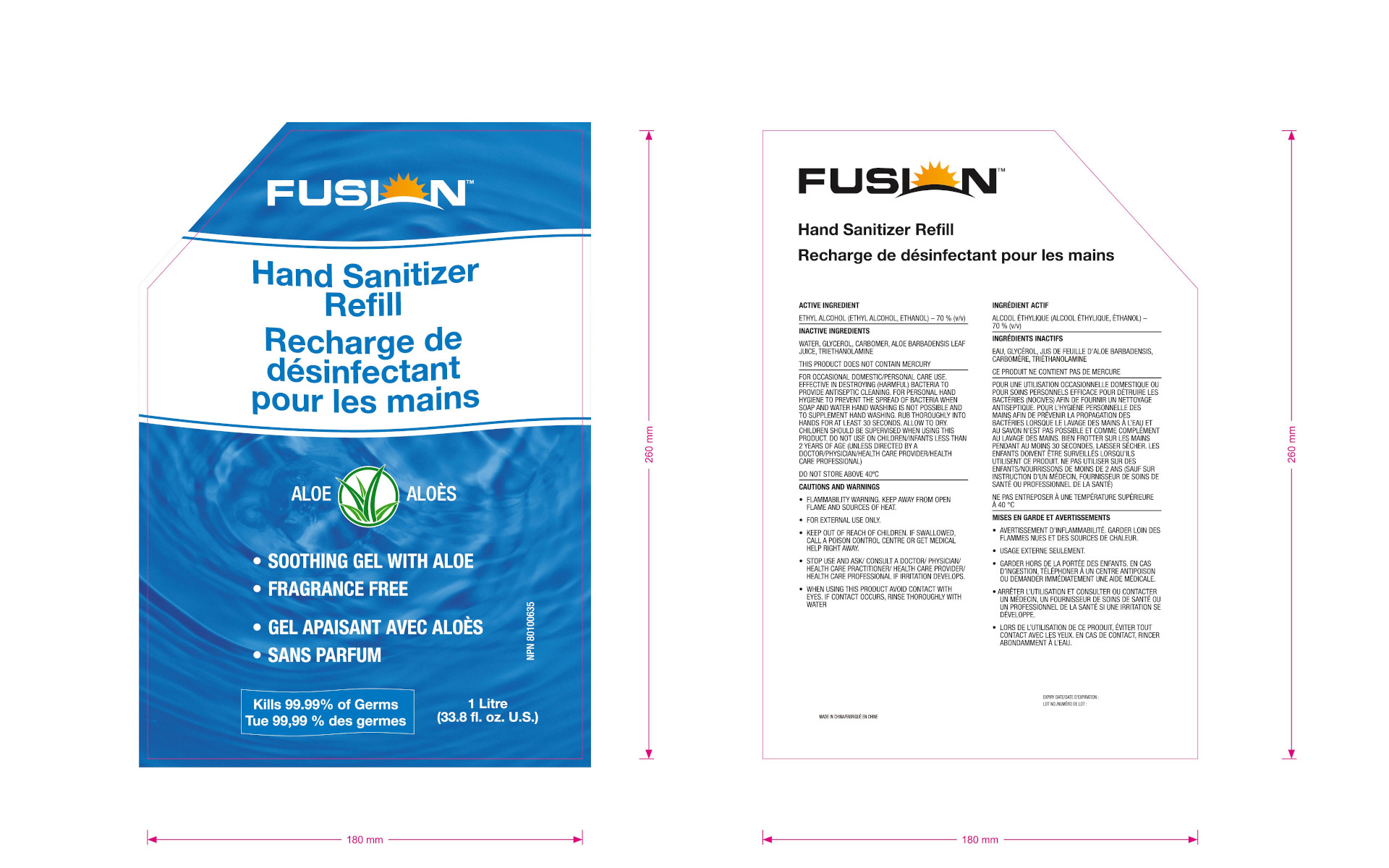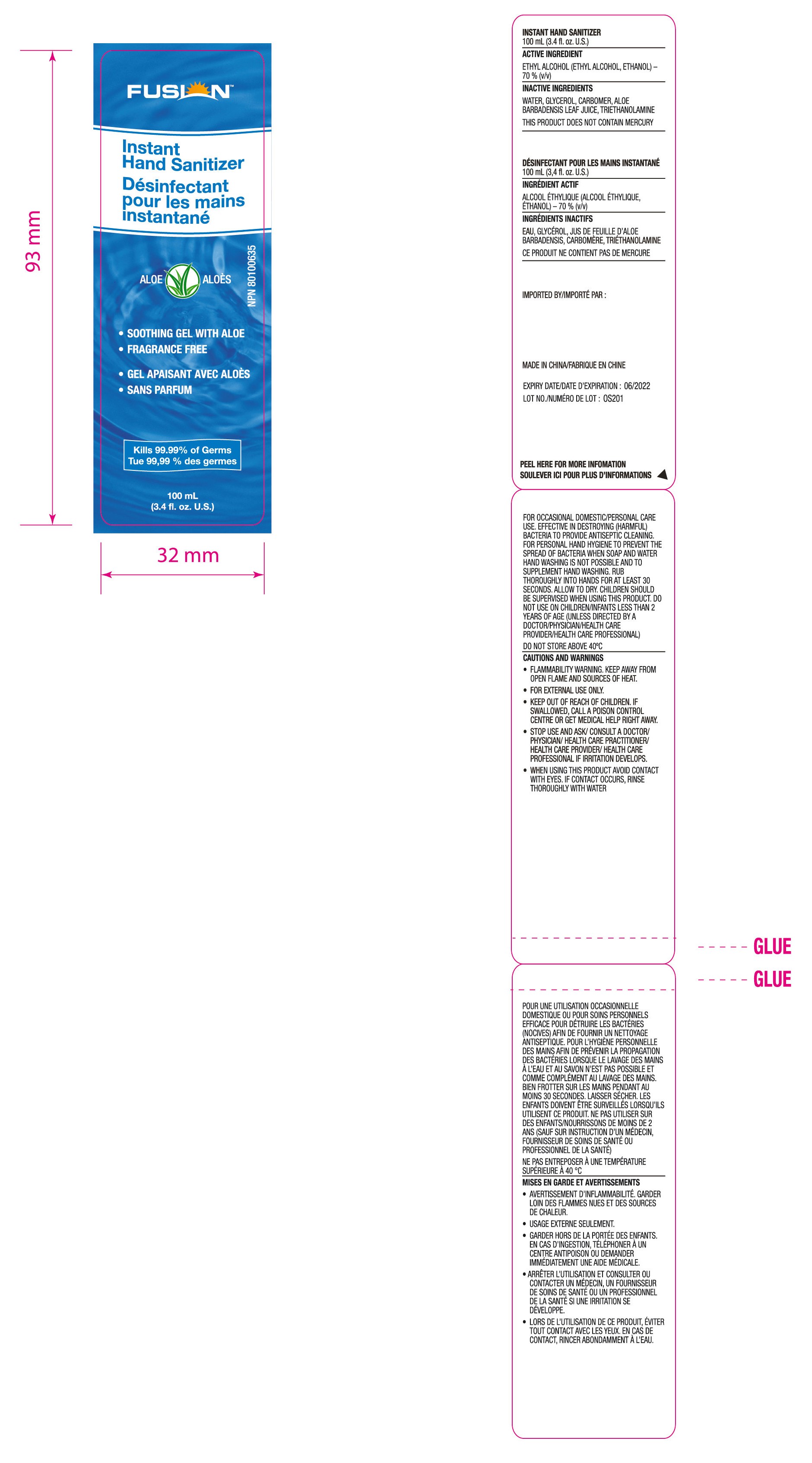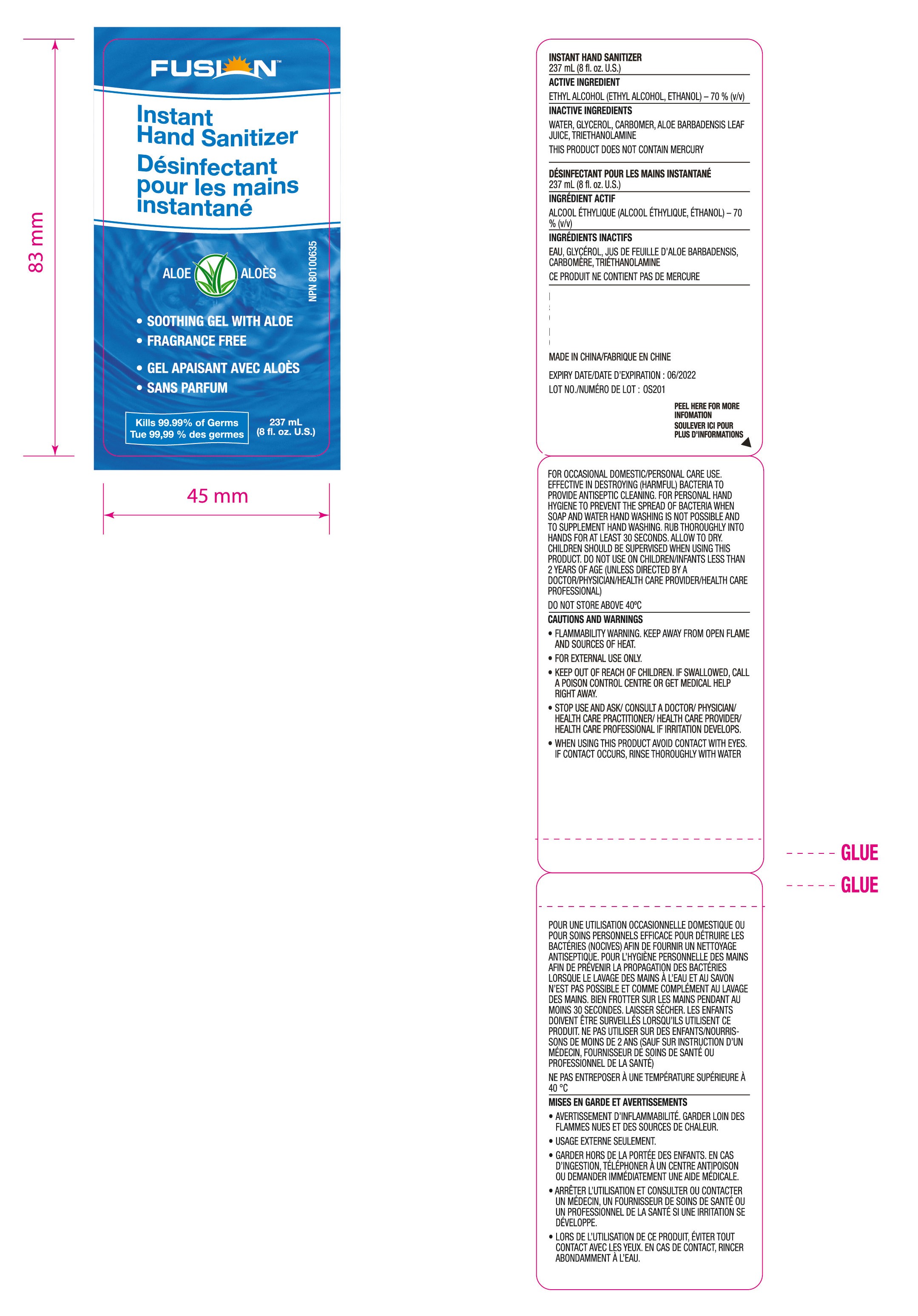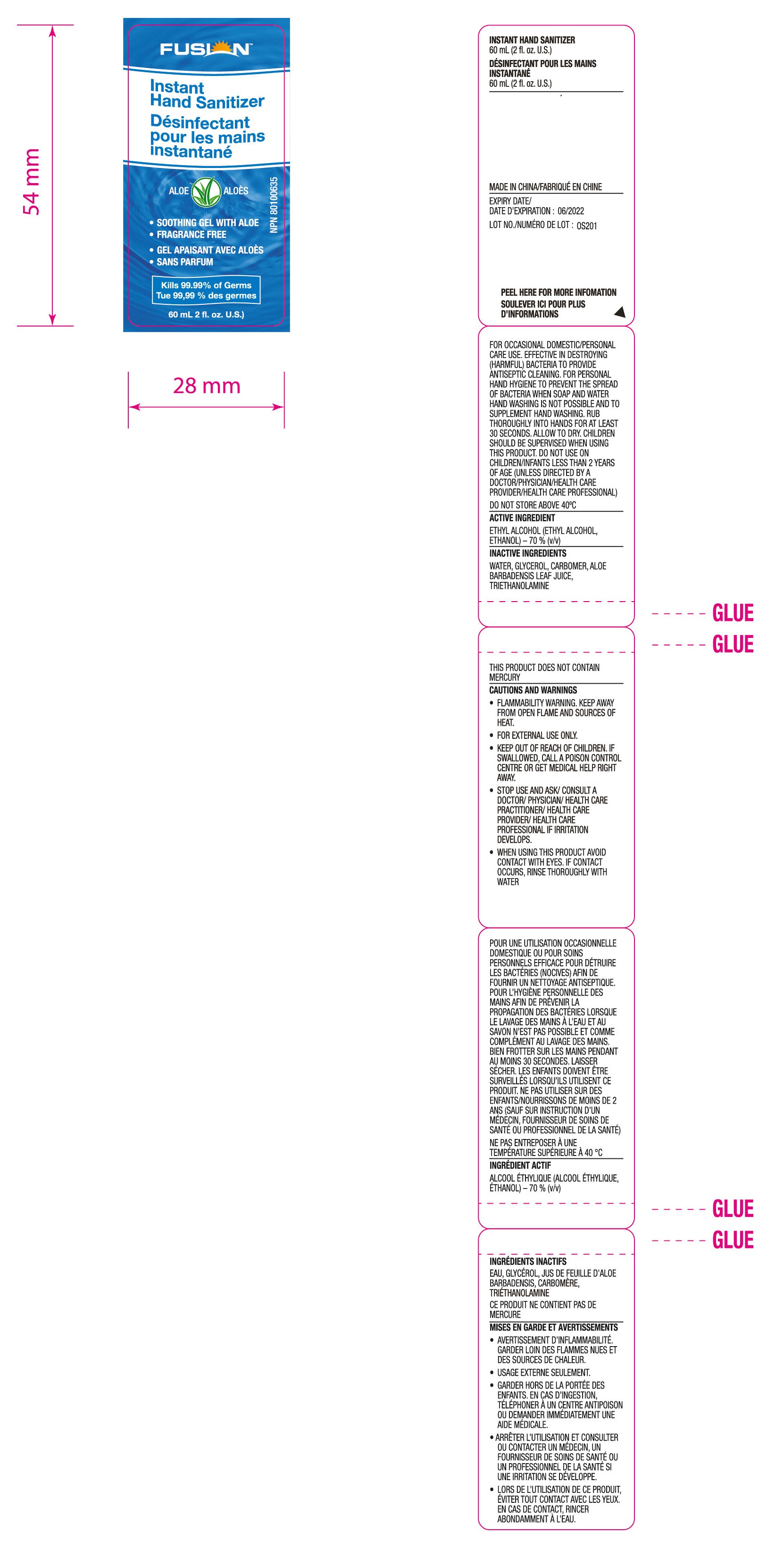 DRUG LABEL: HAND SANITIZER
NDC: 47993-265 | Form: GEL
Manufacturer: NINGBO JIANGBEI OCEAN STAR TRADING CO.,LTD
Category: otc | Type: HUMAN OTC DRUG LABEL
Date: 20201104

ACTIVE INGREDIENTS: ALCOHOL 70 mL/100 mL
INACTIVE INGREDIENTS: CARBOMER 940; ALOE VERA LEAF; WATER; GLYCERIN; TRIETHANOLAMINE BENZOATE

47993-265

INDICATIONS AND USAGE

For personal hand hygiene to prevent the spread of bacteria when soap and water hand washing is not possible and to supplement hand washing.

Directions:

Rub thoroughly into hands for at least 30 seconds. Allow to dry. Children Should be supervised when using this product. Do not use on children/infants less than 2 years of age (unless directed by a doctor/physician/health care provider/health care professional).

OTHER SAFETY INFORMATION

Do not store avove 40℃.

Active ingredients

Ethyl Alcohol (Ethyl alcohol, ethanol) - 70%(v/v)

PURPOSE

For occasional domestic/personal care use.Effective in destroying(harmful)bacteria to provide antiseptic cleaning.

Cautions and warnings

- Flammability warning. Keep away from open flame and sources of heat.
- For external use only.

Keep out of reach of children. If swallowed,call a poison control center or get medical help right away.

Stop use and ask/consult a doctor/physician/health care practitioner/health care provide/health care professional if irritation develops.

When using this product avoid contact with eyes. if contact occurs, rinse thoroughly with water

Inactive Ingredients:

Water,Glycerol,Carbomer,Aloe Barbadensis Leaf Juice,Triethanolamine